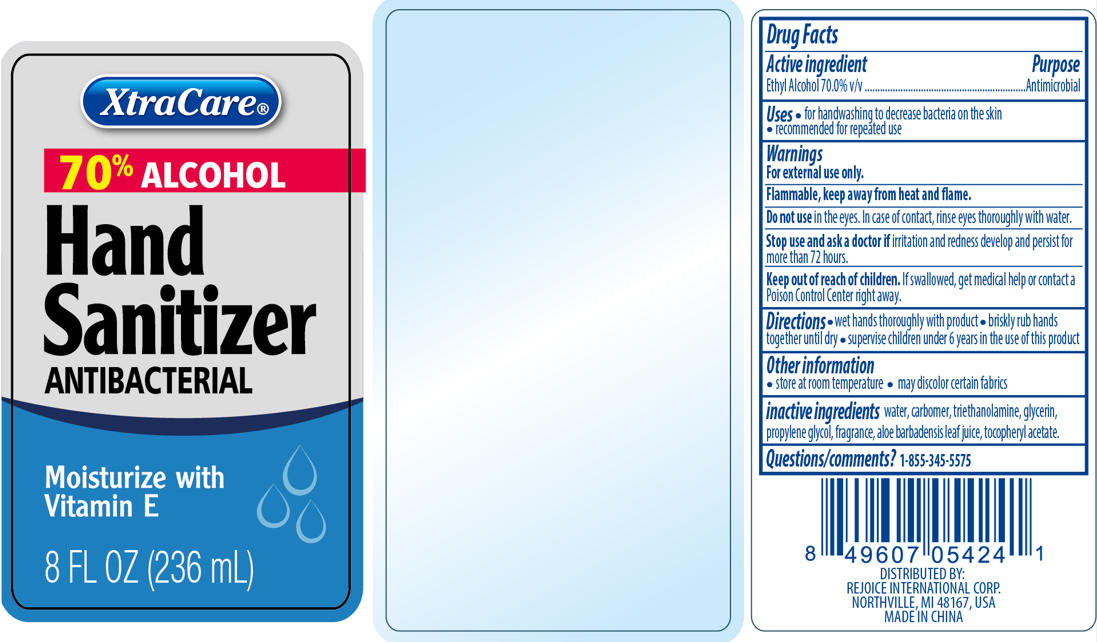 DRUG LABEL: Hand Sanitizer 8 oz. Vitamin E
NDC: 57337-115 | Form: LIQUID
Manufacturer: Ningbo Rejoice International
Category: otc | Type: HUMAN OTC DRUG LABEL
Date: 20260205

ACTIVE INGREDIENTS: ALCOHOL 70 mL/100 mL
INACTIVE INGREDIENTS: PROPYLENE GLYCOL; CARBOMER HOMOPOLYMER, UNSPECIFIED TYPE; TROLAMINE; GLYCERIN; WATER; ALPHA-TOCOPHEROL ACETATE; ALOE VERA LEAF

05424 #-Hand sanitizer 8 oz vitamin E

ACTIVE INGREDIENT

Ethyl Alcohol 70.0% v/v

PURPOSE

Antimicrobial

INDICATIONS AND USAGE

- For handwashing to decrease bacteria on the skin
- Recommended for repeated use

WARNINGS

For external use only.

Flammable, keep away from fire or flame.

Do not use in the eyes. In case of contact, rinse eyes thoroughly with water.

Stop use and ask a doctor if irritation and redness develop and persist for more than 72 hours.

Keep out of reach of children. If swallowed, get medical help or contact a Poison Control Center right away.

DOSAGE AND ADMINISTRATION

- Wet hands thoroughly with product
- Briskly rub hands together until dry
- Supervise children under 6 years in the use of this product

Other Information

- store at room temperature
- may discolor certain fabrics

INACTIVE INGREDIENT

water, glycerin, carbomer, fragrance, triethanolamine, propylene glycol, tocopheryl acetate,